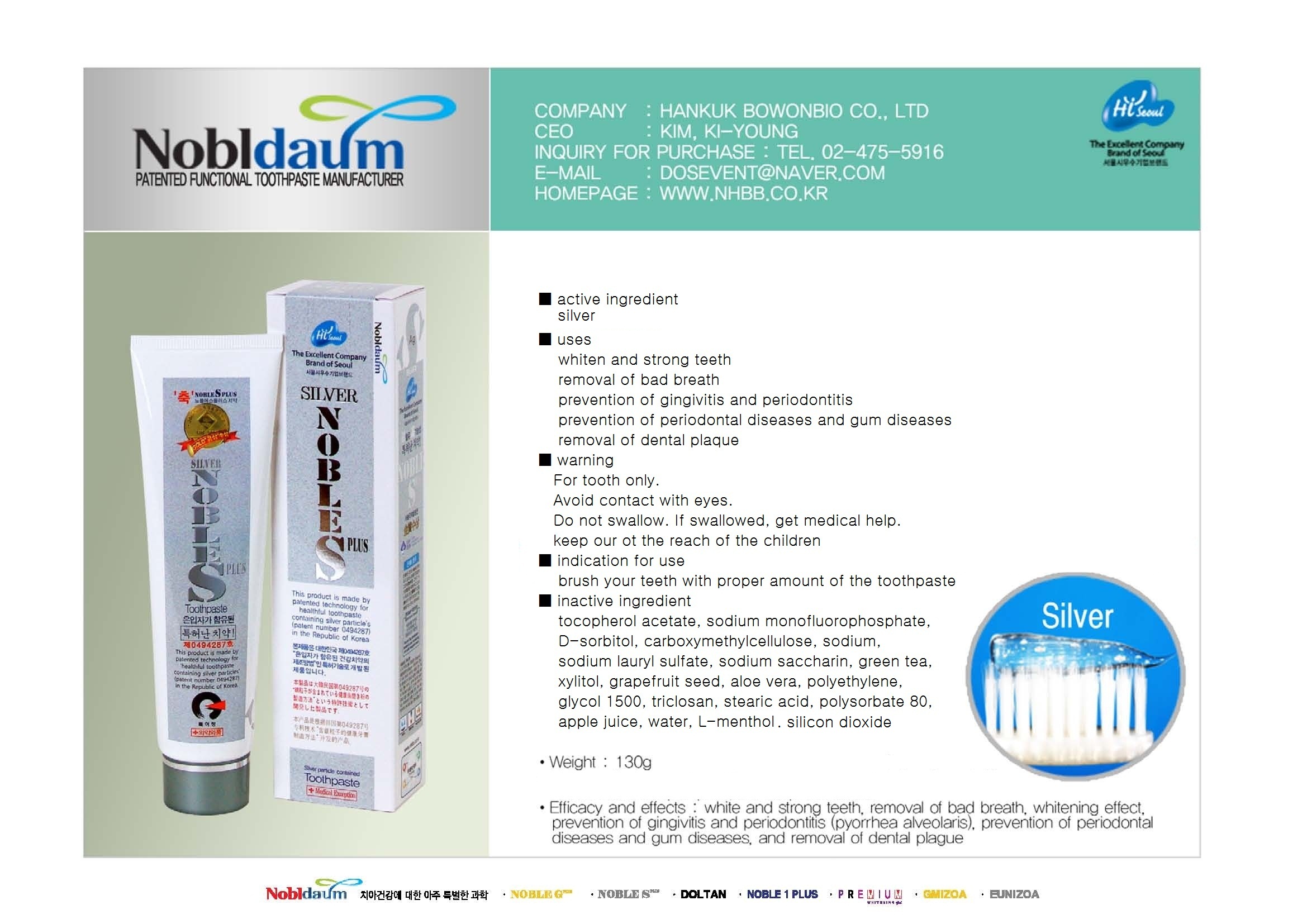 DRUG LABEL: Noble S Plus
NDC: 60319-2001 | Form: PASTE, DENTIFRICE
Manufacturer: Hankuk Bowonbio Co., Ltd
Category: otc | Type: HUMAN OTC DRUG LABEL
Date: 20191203

ACTIVE INGREDIENTS: SILVER 0.7 g/100 g
INACTIVE INGREDIENTS: ALPHA-TOCOPHEROL ACETATE; SODIUM MONOFLUOROPHOSPHATE; SORBITOL; CARBOXYMETHYLCELLULOSE SODIUM; SODIUM LAURYL SULFATE; SACCHARIN SODIUM; GREEN TEA LEAF; XYLITOL; GRAPEFRUIT SEED OIL; ALOE VERA LEAF; POLYETHYLENE GLYCOL 1500; TRICLOSAN; STEARIC ACID; POLYSORBATE 80; APPLE JUICE; LEVOMENTHOL; WATER; SILICON DIOXIDE

Drug Facts

active ingredient: silver<text><content
styleCode="xmChange">
</content></text>

inactive ingredient: tocopherol acetate, sodium monofluorophosphate, D-sorbitol, carboxymethylcellulose sodium, sodium lauryl sulfate, sodium saccharin, green tea, xylitol, grapefruit seed, aloe vera, polyethylene glycol 1500, triclosan, stearic acid, polysorbate 80, apple juice, water, L-menthol, silicon dioxide<text><content
styleCode="xmChange">
</content></text>

PURPOSE

whiten and strong teeth
removal of bad breath
prevention of gingivitis and periodontitis
prevention of periodontal diseases and gum diseases
removal of dental plaque<text><content
styleCode="xmChange">
</content></text>

KEEP OUT OF REACH OF CHILDREN

keep out of reach of the children<text><content
styleCode="xmChange">
</content></text>

INDICATIONS AND USAGE

apply Proper Amount of the toothpaste on the tooth.

WARNINGS

■ For tooth only.
■ Avoid contact with eyes.
■ Do not swallow. If swallowed, get medical help.<text><content
styleCode="xmChange">
</content></text>

DOSAGE AND ADMINISTRATION

brush your teeth by putting appropriate amount of tooth paste<text><content
styleCode="xmChange">
</content></text>